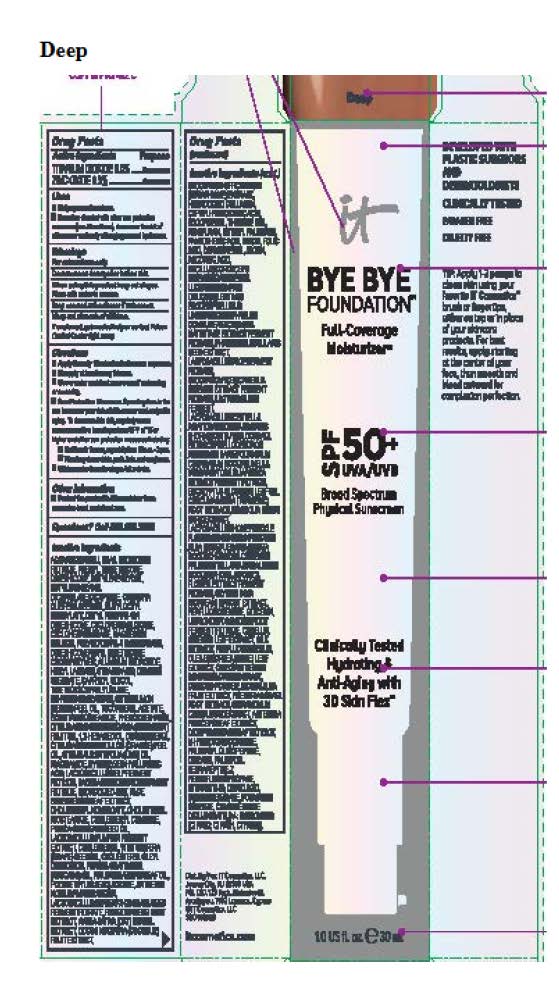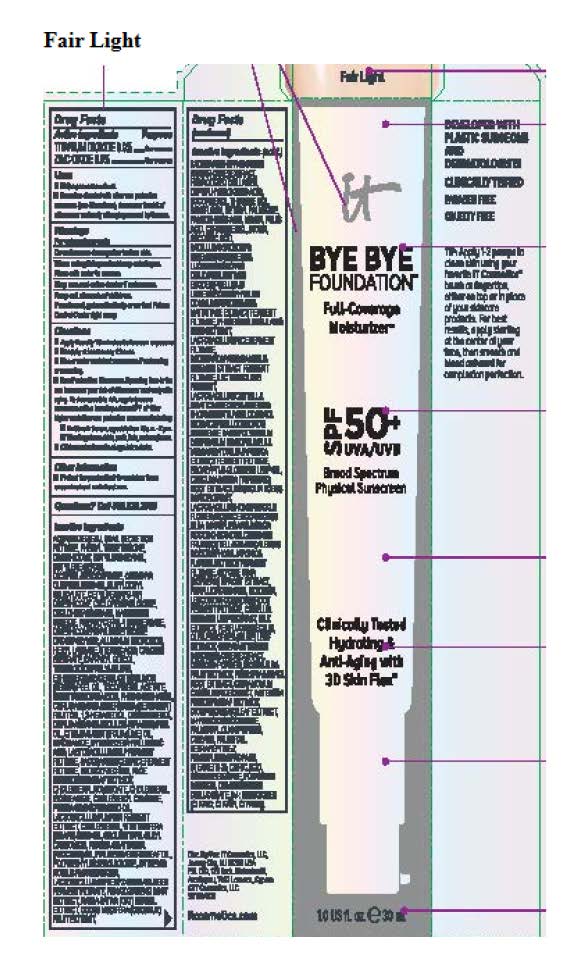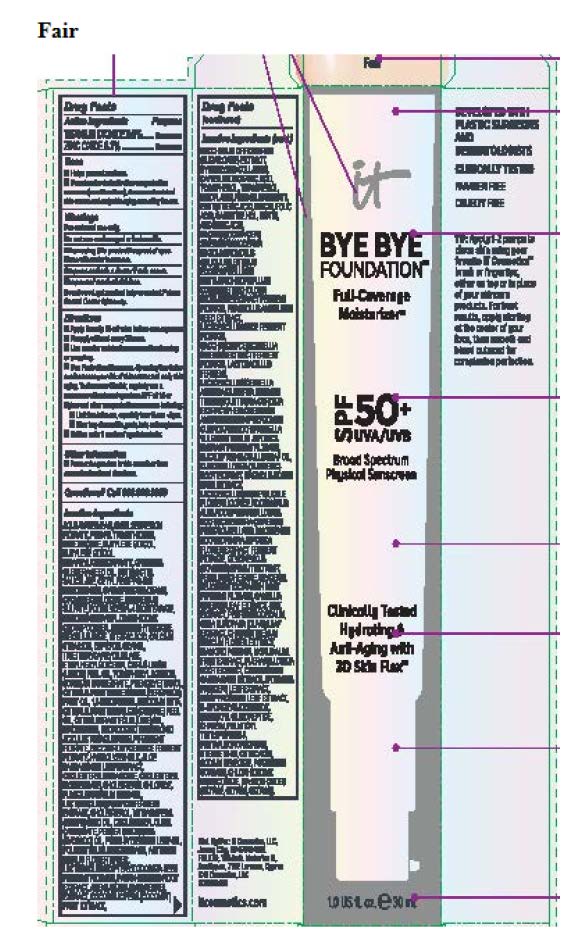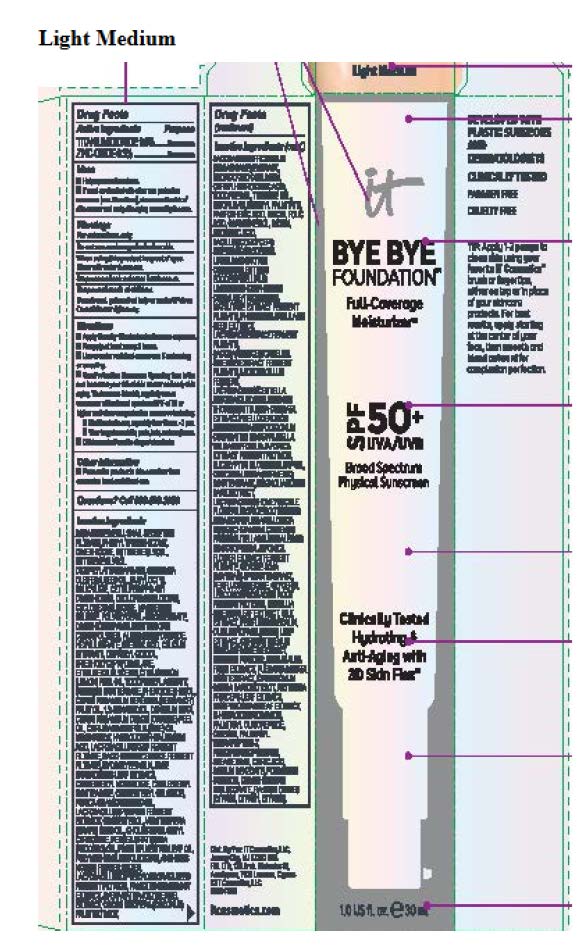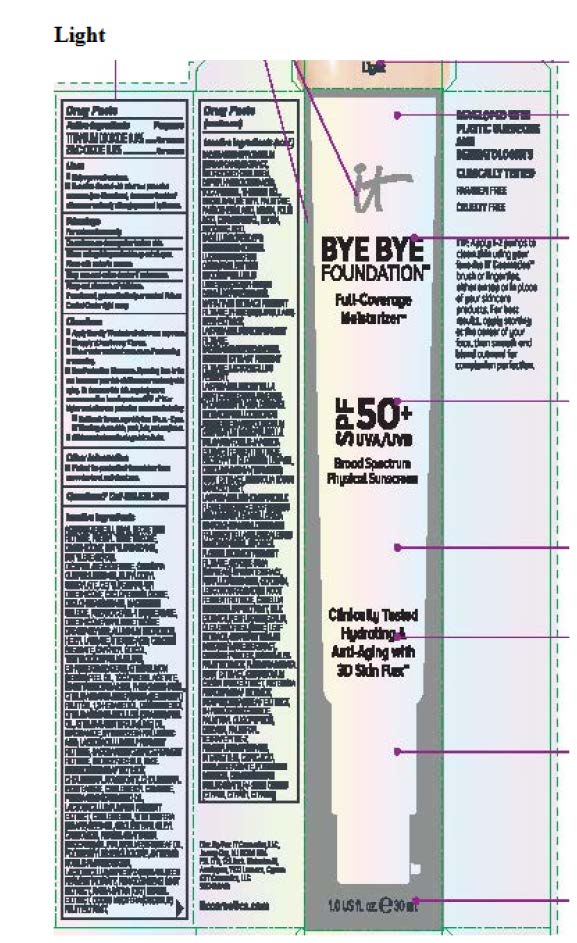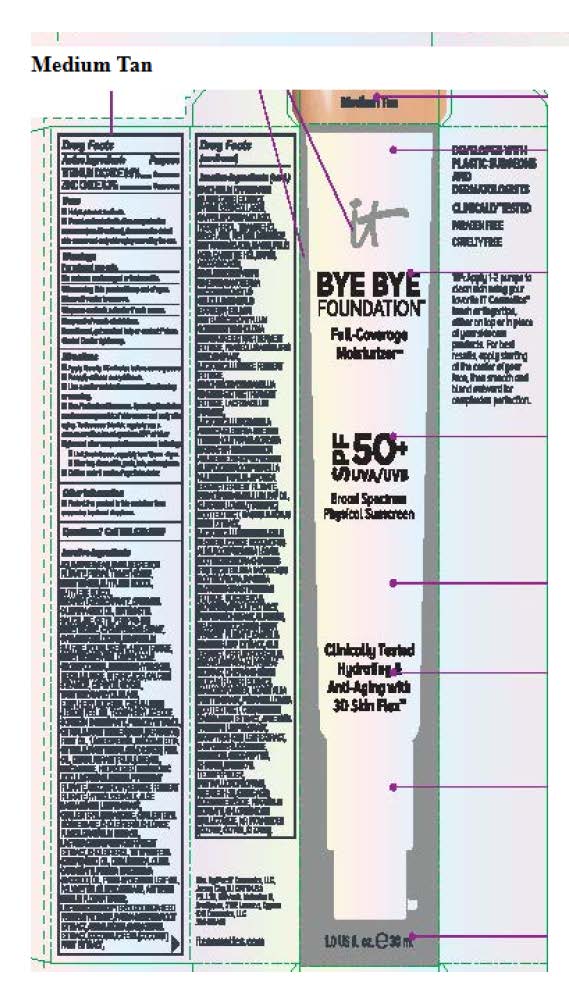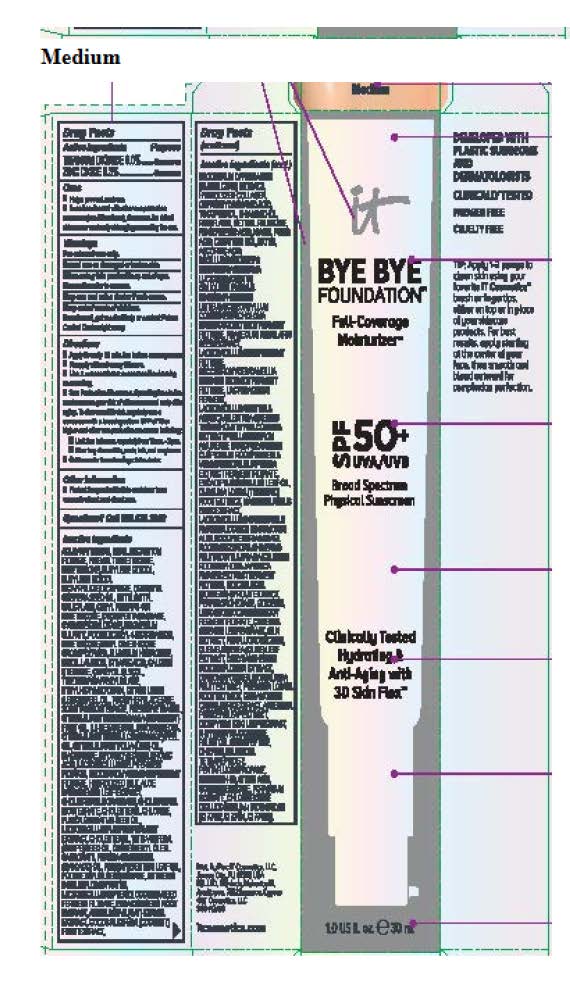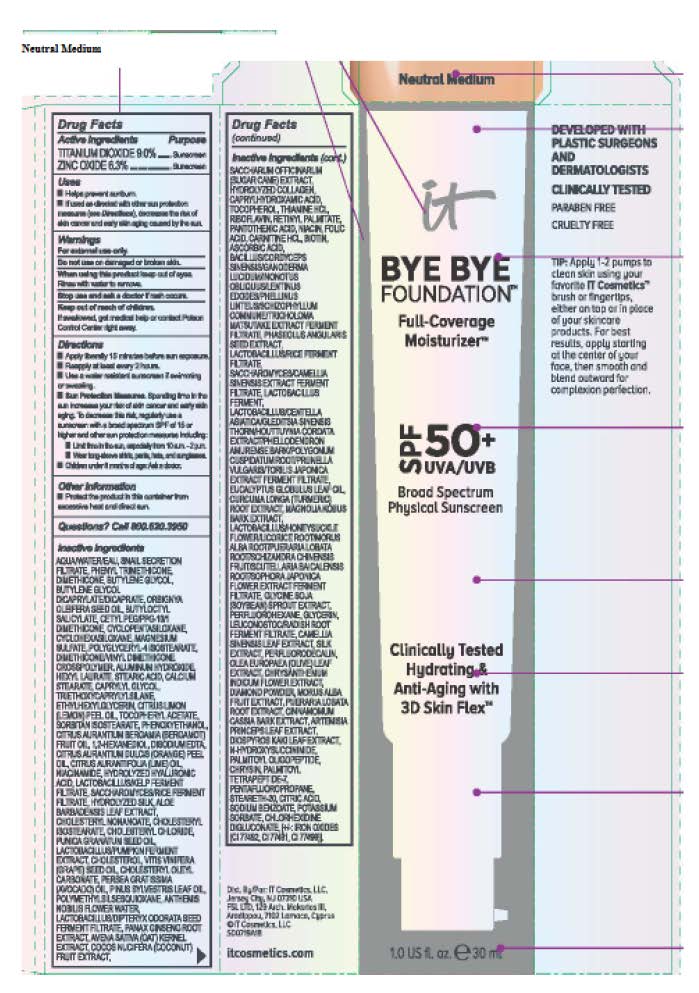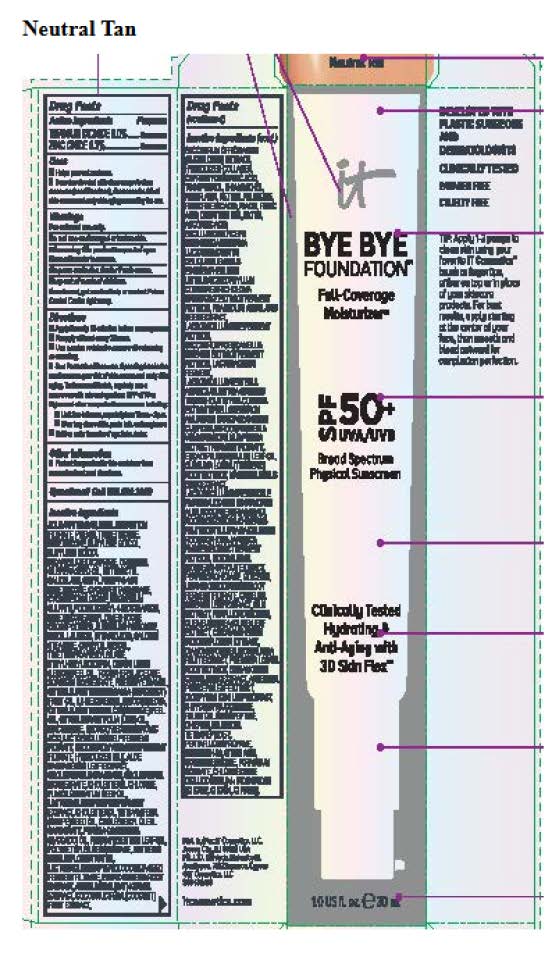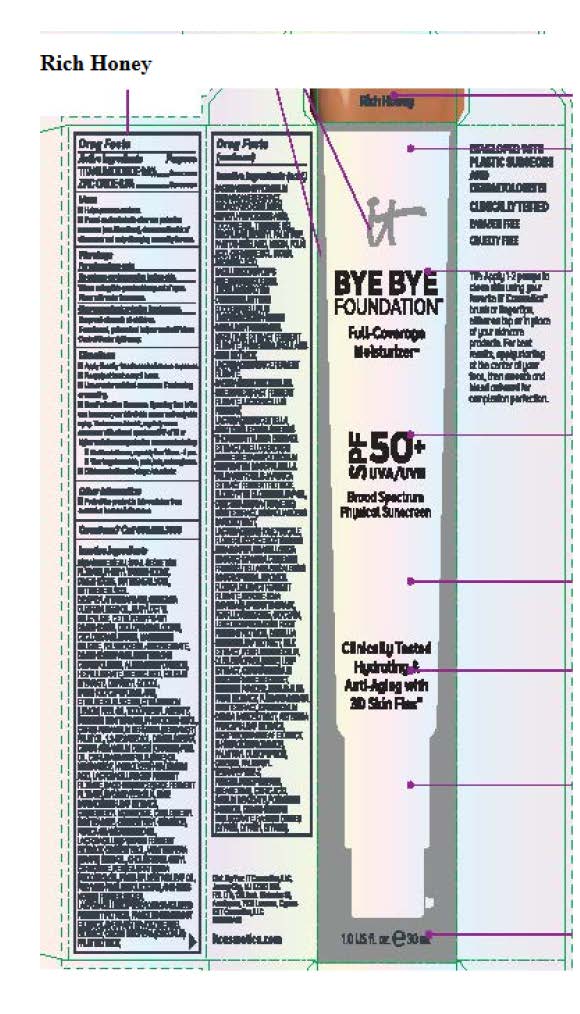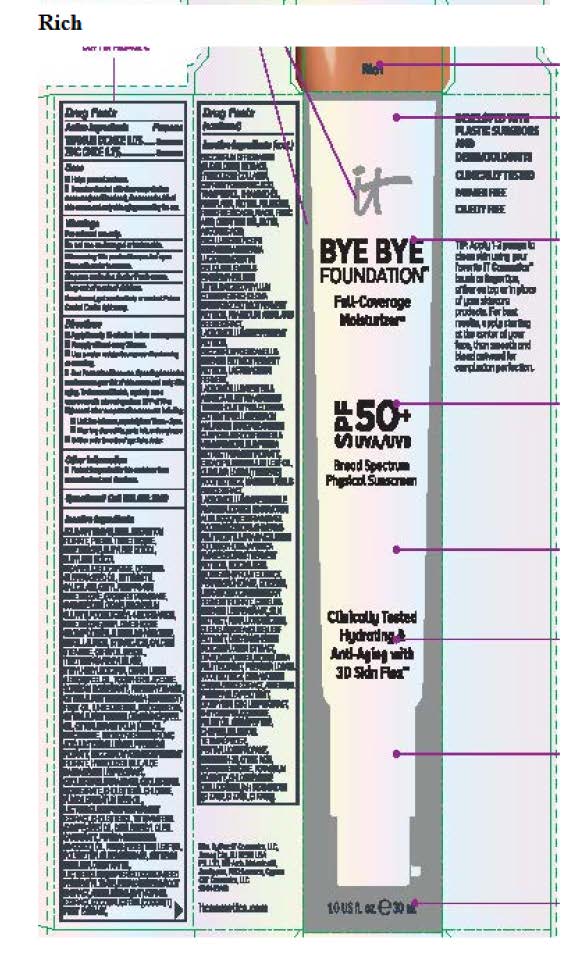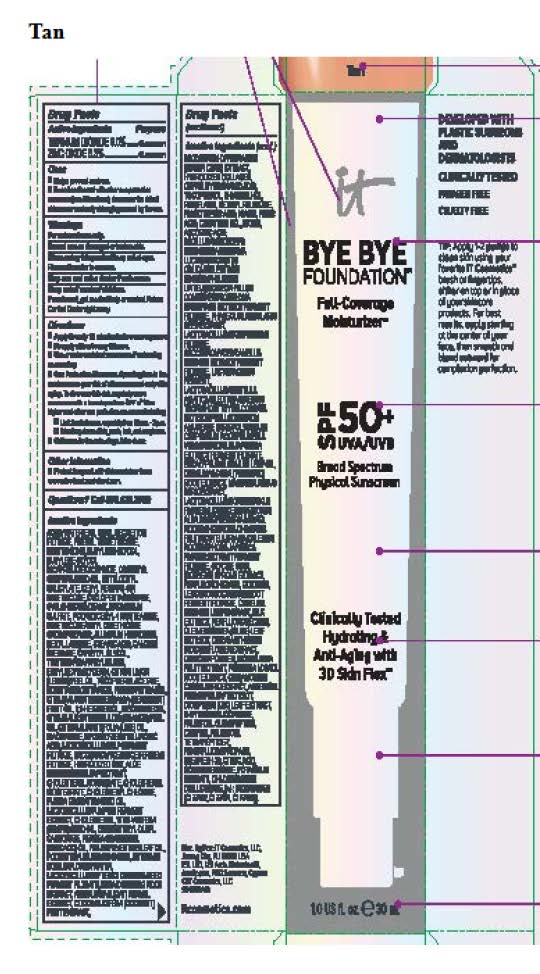 DRUG LABEL: Bye Bye Foundation Full Coverage Moisturizer SPF 50

NDC: 69259-0405 | Form: CREAM
Manufacturer: IT COSMETICS, LLC
Category: otc | Type: HUMAN OTC DRUG LABEL
Date: 20251218

ACTIVE INGREDIENTS: TITANIUM DIOXIDE 9 g/100 mL; ZINC OXIDE 6.3 g/100 mL
INACTIVE INGREDIENTS: WATER; BUTYLENE GLYCOL; PHENYL TRIMETHICONE; BUTYLENE GLYCOL DICAPRYLATE/DICAPRATE; BUTYLOCTYL SALICYLATE; MAGNESIUM SULFATE, UNSPECIFIED FORM; POLYGLYCERYL-4 ISOSTEARATE; ALUMINUM HYDROXIDE; HEXYL LAURATE; STEARIC ACID; CALCIUM STEARATE; CAPRYLYL GLYCOL; TRIETHOXYCAPRYLYLSILANE; ETHYLHEXYLGLYCERIN; SORBITAN ISOSTEARATE; PHENOXYETHANOL; 1,2-HEXANEDIOL; MAGNESIUM DISODIUM EDTA; LIME OIL; GRAPE SEED OIL; PUNICA GRANATUM SEED OIL; AVOCADO OIL; NIACINAMIDE; WHITE PINE OIL; GRAPEFRUIT OIL; CHOLESTEROL; GLYCERIN; EUCALYPTUS OIL; GREEN TEA LEAF; SOYBEAN OIL; PENTAFLUOROPROPANE; TURMERIC; STEARETH-20; SILK, BASE HYDROLYZED (1000 MW); HYALURONIC ACID; OATMEAL; CITRIC ACID MONOHYDRATE; SODIUM BENZOATE; POTASSIUM SORBATE; ALOE VERA LEAF; N-HYDROXYSUCCINIMIDE; HYDROLYSED MARINE COLLAGEN (ENZYMATIC; 2000 MW); CAPRYLHYDROXAMIC ACID; TOCOPHEROL; THIAMINE HYDROCHLORIDE; RIBOFLAVIN; RETINOL; PANTOTHENIC ACID; PALMITOYL OLIGOPEPTIDE; NIACIN; FOLIC ACID; CHRYSIN; CARNITINE HYDROCHLORIDE, (+)-; BIOTIN; ASCORBIC ACID; PALMITOYL TETRAPEPTIDE-7; CHLORHEXIDINE; BROWN IRON OXIDE; CHOLESTERYL OLEYL CARBONATE; CHOLESTERYL NONANOATE; CHOLESTERYL ISOSTEARATE; CHOLESTERYL CHLORIDE

Active ingredients

Titanium dioxide 9.0%
Zinc oxide 6.3%

Purpose

Sunscreen

Uses

• Helps prevent sunburn.
• If used as directed with other sun protection measures (see Directions), decreases the risk of skin cancer and early skin aging caused by the sun.

Warnings

For external use only

Do not use

on damaged or broken skin

When using this product

keep out of eyes. Rinse with water to remove.

Stop use and ask a doctor if

rash occurs

Keep out of reach of children.

If swallowed, get medical help or contact Poison Control Center right away.

Directions

• Apply liberally 15 minutes before sun exposure.
• Reapply at least every 2 hour.
• Use a water resistant sunscreen if swimming or sweating.
• Sun Protection Measures. Spending time in the sun increases your risk of skin cancer and early skin aging. To decrease this risk, regularly use a sunscreen with a Broad Spectrum SPF value of 15 or higher and other sun protection measures including:
• limit time in the sun, especially from 10 a.m.–2 p.m.
• wear long-sleeved shirts, pants, hats, and sunglasses.
Children under 6 months of age: Ask a doctor.

Other information

Protect the product in this container from excessive heat and direct sun.

Inactive ingredients

Water, Snail Secretion Filtrate, Phenyl Trimethicone, Dimethicone, Butylene Glycol, Butylene Glycol Dicaprylate/Dicaprate, Orbignya Oleifera Seed Oil, Butyloctyl Salicylate, Cetyl PEG/PPG-10/1 Dimethicone, Cyclopentasiloxane, Cyclohexasiloxane, Magnesium Sulfate, Aluminum Hydroxide, Stearic Acid, Polyglyceryl-4 Isostearate, Dimethicone/Vinyl Dimethicone Crosspolymer, Hexyl Laurate, Calcium Stearate, Caprylyl Glycol, Triethoxycaprylylsilane, Ethylhexylglycerin, Citrus Medica Limonum (Lemon) Peel Oil, Tocopheryl Acetate, Sorbitan Isostearate, Phenoxyethanol, Citrus Aurantium Bergamia (Bergamot) Fruit Oil, 1,2-Hexanediol, Disodium EDTA, Citrus Aurantium Dulcis (Orange) Peel Oil, Citrus Aurantifolia (Lime) Oil, Cholesterol, Persea Gratissima (Avocado) Oil, Cholesteryl Oleyl Carbonate, Pinus Sylvestris Leaf Oil, Niacinamide, Punica Granatum Seed Oil, Vitis Vinifera (Grape) Seed Oil, Lactobacillus/Pumpkin Ferment Extract, Polymethylsilsesquioxane, Anthemis Nobilis Flower Water, Lactobacillus/Dipteryx Odorata Seed Ferment Filtrate, Avena Sativa (Oat) Kernel Extract, Panax Ginseng Root Extract*, Eucalyptus Globulus Leaf Oil, Saccharomyces/Rice Ferment Filtrate, Lactobacillus/Kelp Ferment Filtrate, Cholesteryl Nonanoate, Cholesteryl Isostearate, Cholesteryl Chloride, Curcuma Longa (Turmeric) Root Extract, Lactobacillus/Honeysuckle Flower/Licorice Root/Morus Alba Root/Pueraria Lobata Root/Schizandra Chinensis Fruit/Scutellaria Baicalensis Root/Sophora Japonica Flower Extract Ferment Filtrate, Magnolia Kobus Bark Extract, Glycine Soja (Soybean) Sprout Extract, Perfluorohexane, Glycerin, Leuconostoc/Radish Root Ferment Filtrate, Camellia Sinensis Leaf Extract, Hydrolyzed Silk, Perfluorodecalin, Silk Extract, Olea Europaea (Olive) Leaf Extract, Pentafluoropropane, Steareth-20, Citric Acid, Cocos Nucifera (Coconut) Fruit Extract, Saccharum Officinarum (Sugar Cane) Extract, Hydrolyzed Collagen, Lactobacillus/Rice Ferment Filtrate, Lactobacillus/Centella Asiatica/Gleditsia Sinensis Thorn/Houttuynia Cordata Extract/Phellodendron Amurense Bark/Polygonum Cuspidatum Root/Prunella Vulgaris/Torilis Japonica Extract Ferment Filtrate, Lactobacillus Ferment, Bacillus/Cordyceps Sinensis/Ganoderma Lucidum/Inonotus Obliquus/Lentinus Edodes/Phellinus Linteus/Schizophyllum Commune/Tricholoma Matsutake Extract Ferment Filtrate, Phaseolus Angularis Seed Extract, Saccharomyces/Camellia Sinensis Extract Ferment Filtrate, Sodium Benzoate, Potassium Sorbate, Chrysanthemum Indicum Flower Extract, Diamond Powder, Caprylhydroxamic Acid, Artemisia Princeps Leaf Extract, Cinnamomum Cassia Bark Extract, Diospyros Kaki Leaf Extract, Morus Alba Fruit Extract, Aloe Barbadensis Leaf Extract, N-Hydroxysuccinimide, Pantothenic Acid, Biotin, Thiamine HCl, Retinyl Palmitate, Tocopherol, Niacin, Carnitine HCl, Ascorbic Acid, Riboflavin, Folic Acid, Palmitoyl Oligopeptide, Chrysin, Hydrolyzed Hyaluronic Acid, Palmitoyl Tetrapeptide-7, Chlorhexidine digluconate, Iron Oxides (CI 77492, CI 77491, CI 77499).

Questions?

Call 800.620.3950